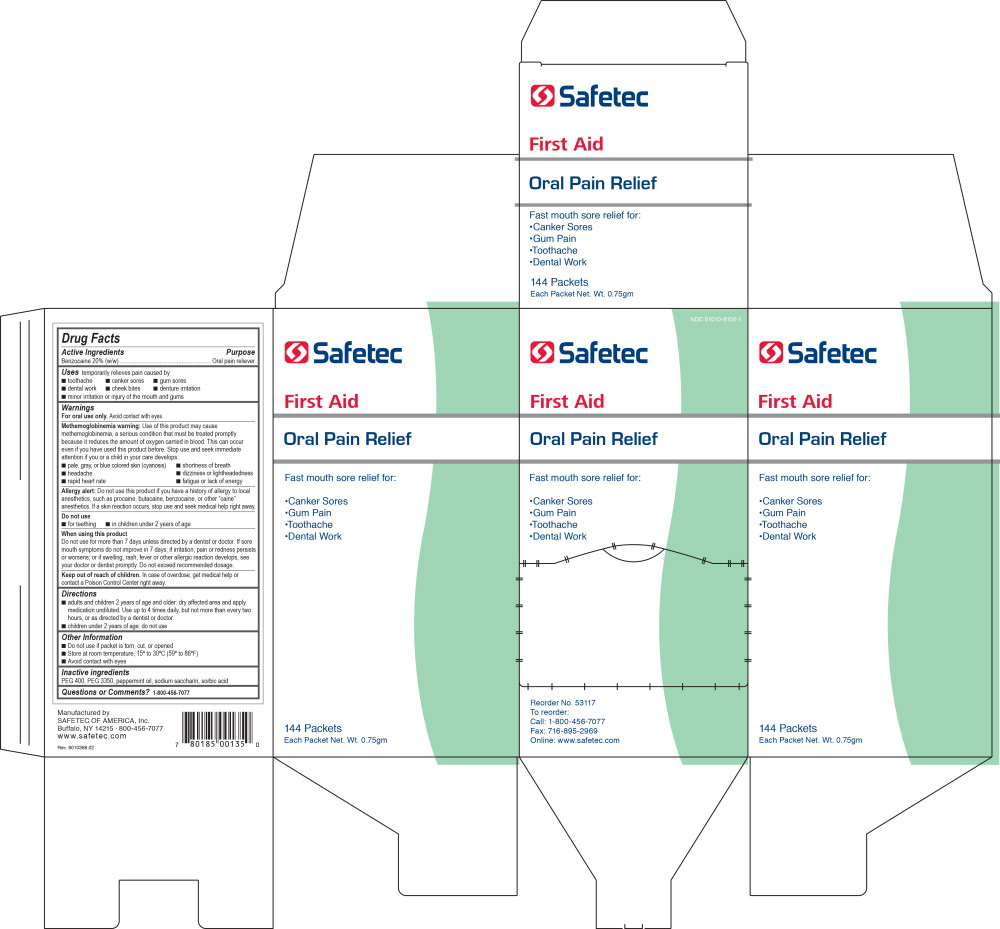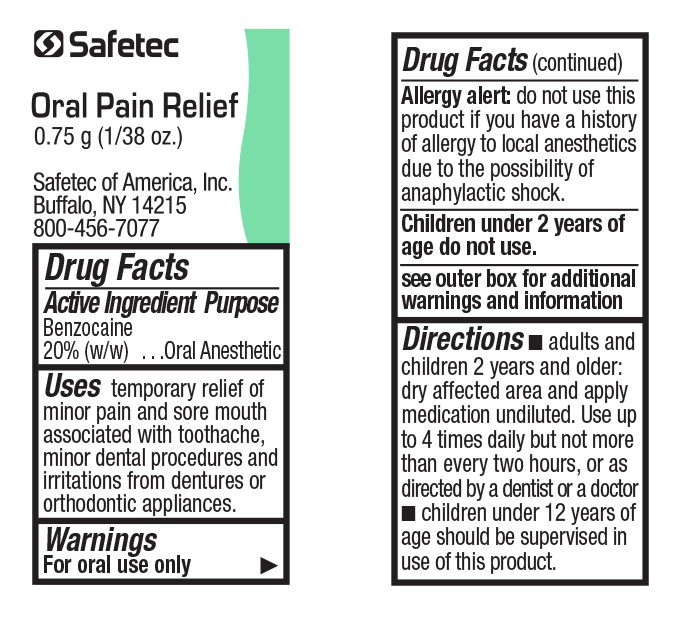 DRUG LABEL: Pain Relief
NDC: 61010-8100 | Form: LIQUID
Manufacturer: Safetec of America, Inc.
Category: otc | Type: HUMAN OTC DRUG LABEL
Date: 20240216

ACTIVE INGREDIENTS: BENZOCAINE
 200 mg/1 g
INACTIVE INGREDIENTS: POLYETHYLENE GLYCOL 400; POLYETHYLENE GLYCOL 3350; PEPPERMINT OIL; SACCHARIN SODIUM; SORBIC ACID

61010-8100-1,-2, Pain Relief

Active Ingredients

Benzocaine 20% (w/w)

Purpose

Oral pain reliever

Uses

temporarily relieves pain caused by

- toothache
- dental work
- minor irritation or injury of the mouth and gums
- canker sores
- gum sores
- cheek bites
- denture irritation

Warnings

For oral use only.Avoid contact with eyes.

Methemoglobinemia warning:Use of this product may cause methemoglobinemia, a serious condition that must be treated promptly because it reduces the amount of oxygen carried in blood. This can occur even if you have used this product before. Stop use and seek immediate attention if you or a child in your care develops:

- pale, gray, or blue colored skin (cyanosis)
- headache
- rapid heart rate
- shortness of breath
- dizziness or lightheadedness
- fatigue or lack of energy

Allergy alert:Do not use this product if you have a history of allergy to local anesthetics, such as procaine, butacaine, benzocaine, or other “caine” anesthetics. If a skin reaction occurs, stop use and seek medical help right away.

Do not use

- for teething
- in children under 2 years of age

When using this product

Do not use for more than 7 days unless directed by a dentist or doctor. If sore mouth symptoms do not improve in 7 days; if irritation, pain or redness persists or worsens; or if swelling, rash, fever or other allergic reaction develops, see your doctor or dentist promptly. Do not exceed recommended dosage.

Keep out of reach of children.In case of overdose, get medical help or contact a Poison Control Center right away.

Directions

- adults and children 2 years of age and older: dry affected area and apply medication undiluted. Use up to 4 times daily, but not more than every two hours, or as directed by a dentist or doctor.
- children under 2 years of age: do not use

Other Information

- Do not use if packet is torn, cut, or opened
- Store at room temperature, 15º to 30ºC (59º to 86ºF)
- Avoid contact with eyes

Inactive ingredients

PEG 400, PEG 3350, peppermint oil, sodium saccharin, sorbic acid

Questions or Comments?

1-800-456-7077

Principal Display Panel - Safetec Oral Pain Relief Carton Label

NDC 61010-800-1

Safetec

First Aid

Oral Pain Relief

Fast mouth sore relief for:

Canker Sores

Gum Pain

Toothache

Dental Work

Reorder No. 53117

To reorder:

Call: 1-800-456-7077

Fax: 716-895-2969

Online: www.safetec.com

Principal Display Panel - Safetec Oral Pain Relief Packet Label

Safetec

Oral Pain Relief

0.75 g (1/38 oz.)

Safetec of America, Inc.

Buffalo, NY 14215

800-456-7077